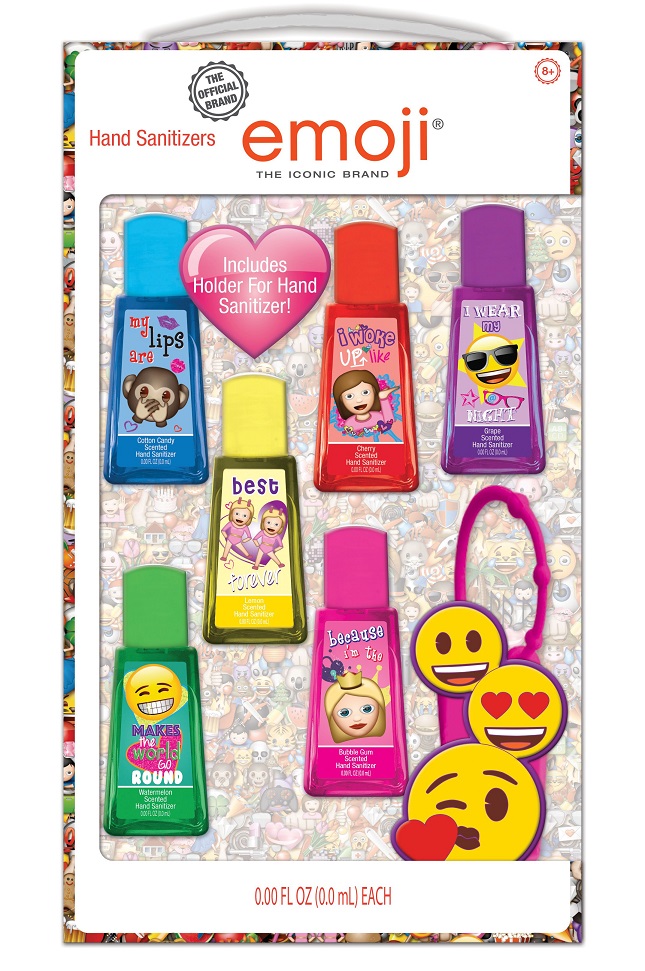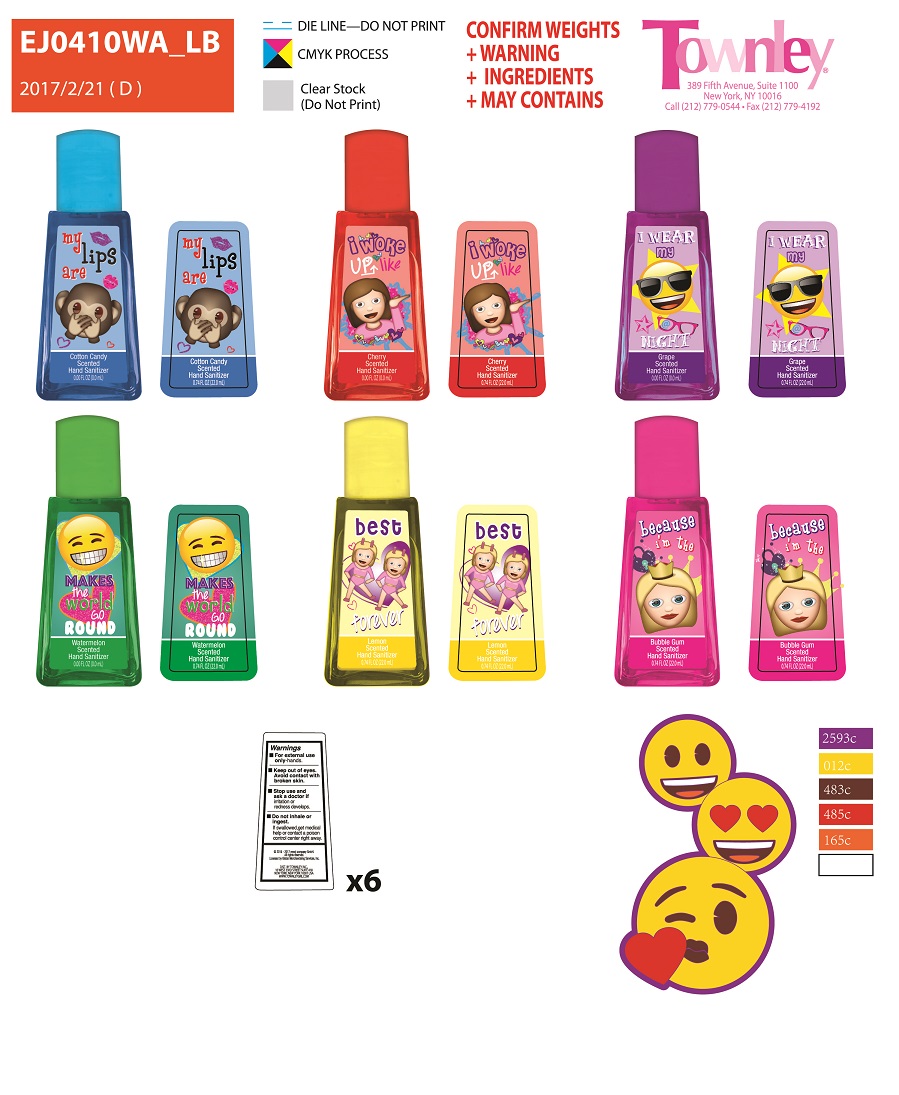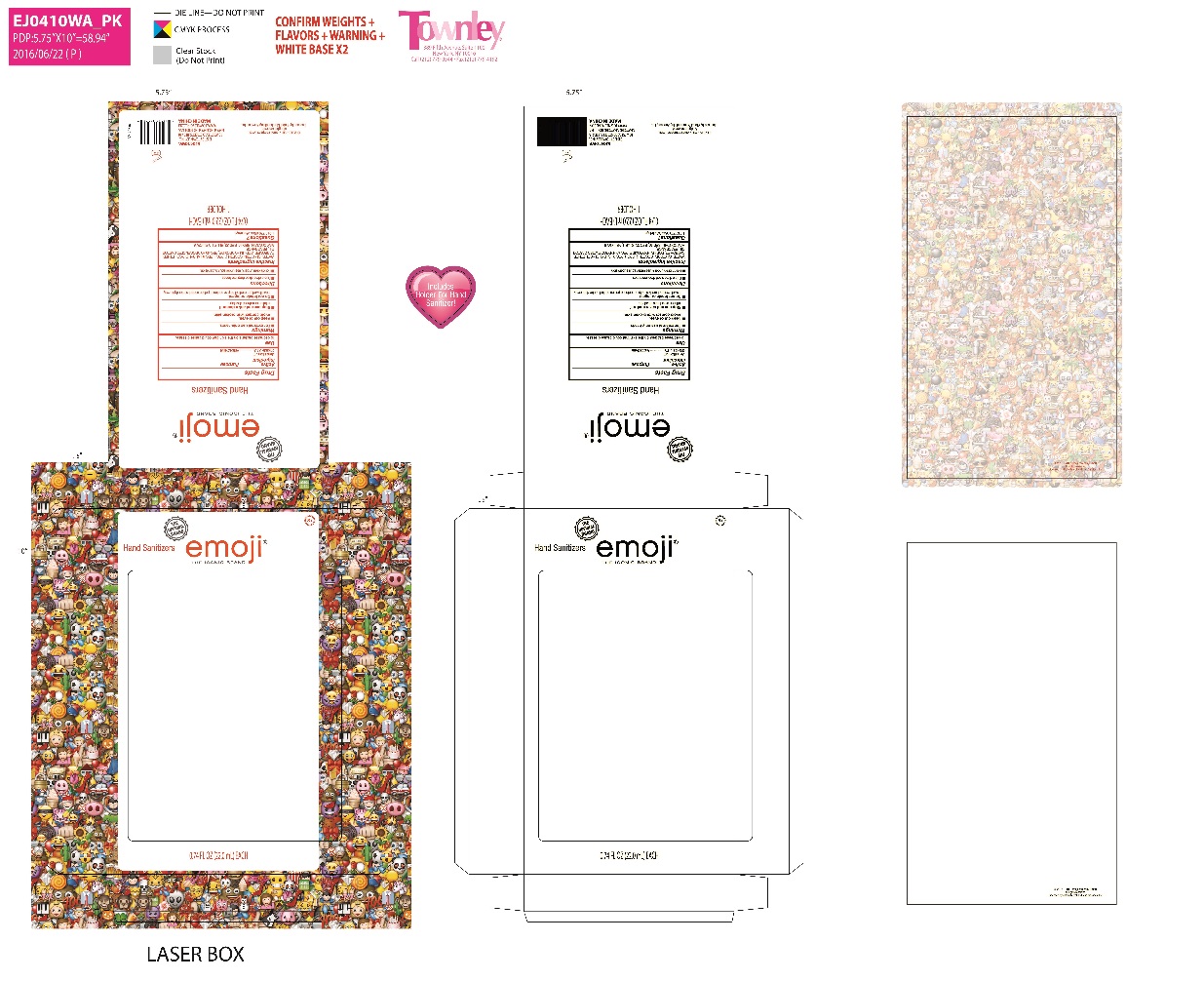 DRUG LABEL: Emoji 6 pack Scented Hand Sanitizer
NDC: 54860-086 | Form: GEL
Manufacturer: Shenzhen Lantern Science Co., Ltd.
Category: otc | Type: HUMAN OTC DRUG LABEL
Date: 20170718

ACTIVE INGREDIENTS: BENZALKONIUM CHLORIDE 1 g/30 mL
INACTIVE INGREDIENTS: FD&C RED NO. 40; FD&C BLUE NO. 1; D&C RED NO. 33; GLYCERIN; COCETH-7; CARBOXYMETHYL FRAGMENT; PHENOXYETHANOL; PPG-1-PEG-9 LAURYL GLYCOL ETHER; SODIUM HYDROXIDE; FD&C YELLOW NO. 5; WATER; POLYOXYL 40 HYDROGENATED CASTOR OIL

Active Ingredient

Benzalkonium Chloride 0.1%

Purpose: Antibacterial

Use

To decrease bacteria on the skin that could cause disease.

Keep out of reach of children.

Warnings

- for external use only-hands.
- keep out of eyes. avoid contact with broken skin.
- stop use and ask a Doctor if irritation or redness develops.
- do not inhale or ingest. if swallowed, get medical help or contact a poison control center right away.

Directions

- Rub a dime sized drop into hands.
- For children under 6 use under adult supervision.

Inactive Ingredients

water, glycerin, coceth-7, PPG-1-PEG-9 lauryl glycol ether, carbomer, PEG-40 hydrogenated castor oil, fragrance (parfum).

May Contain

Red 40 (CI 16035), Red 33 (CI 17200), Blue 1 (CI 42090), Yellow 5 (CI 19140).

INDICATIONS AND USAGE

Hand Sanitizer